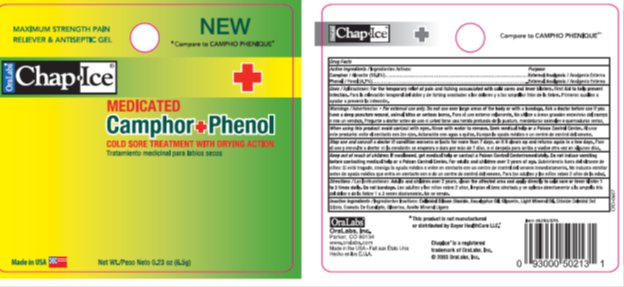 DRUG LABEL: ChapIce Camphor Phenol Gel
NDC: 63645-160 | Form: GEL
Manufacturer: OraLabs
Category: otc | Type: HUMAN OTC DRUG LABEL
Date: 20130729

ACTIVE INGREDIENTS: CAMPHOR (SYNTHETIC) 10.8 mg/1 g; PHENOL 4.7 mg/1 g
INACTIVE INGREDIENTS: LIGHT MINERAL OIL 77.75 mg/1 g; SILICON DIOXIDE 5.75 mg/1 g; GLYCERIN 0.5 mg/1 g; EUCALYPTUS OIL 0.500 mg/1 g

Drug Facts

Active ingredient

Camphor 10.8%, Phenol 4.7%

Purpose

External Analgesic

Keep Out of Reach of Children

If swallowed, get medical help or contact a Poison Control Center immediately. Do not induce vomiting before contacting medical help or a Poison Control Center. For adults and children over 2 years of age.

Uses

For the temporary relief of pain and itching associated with cold sores and fever blisters. First Aid to help prevent infection.

Warnings

For external use only.

Do not use over large areas of the body or with a bandage. Ask a doctor before use if you have a deep puncture wound, animal bites, or serious burns.

When using this product: avoid contact with eyes. Rinse with water to remove. Seek medical help or contact a Poison Control Center.

Stop use and consult a doctor if: conditions worsen or last more than 7 days, or if it clears up and returns again in a few days.

Directions

Adults and children over 2 years clean the affected area and apply directly to a cold sore or fever blister 1 to 3 times daily. Do not bandage.

Inactive Ingredients

Colloidal Silicon Dioxide, Eucalyptus Oil, Glycerin, Light Mineral Oil